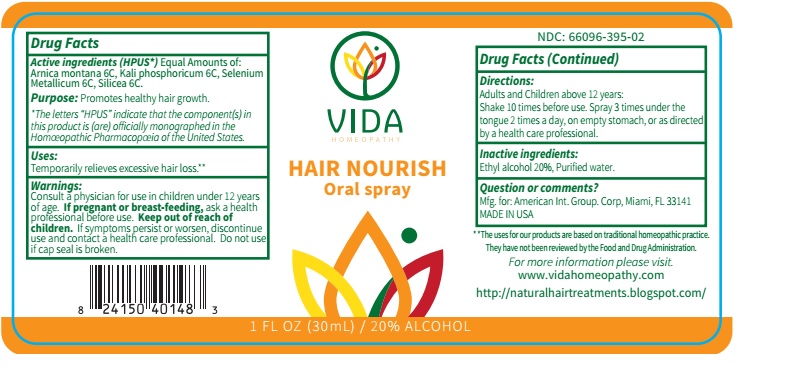 DRUG LABEL: Vida Hair Nourish
NDC: 66096-395 | Form: SPRAY
Manufacturer: OHM PHARMA INC.
Category: homeopathic | Type: HUMAN OTC DRUG LABEL
Date: 20190905

ACTIVE INGREDIENTS: ARNICA MONTANA 6 [hp_C]/30 mL; DIBASIC POTASSIUM PHOSPHATE 6 [hp_C]/30 mL; SELENIUM 6 [hp_Q]/30 mL; SILICON DIOXIDE 6 [hp_C]/30 mL
INACTIVE INGREDIENTS: ALCOHOL; WATER

Vida Hair Nourish Oral Spray

ACTIVE INGREDIENT

Active ingredients (HPUS*) Equal amounts of: Arnica montana 6C, Kali phosphoricum 6C, Selenium Metallicum 6C, Silicea.

*The letters *HPUS* indicate that the component(s) in this product is (are) officially monographed in the Homeopathic Pharmacopeia of the United States.

INDICATIONS AND USAGE

Uses: Temporarily relieves excessive hair loss.**

**The uses for our products are based on traditional homeopathic practice. They have not been reviewed by the Food and Drug Administration.

WARNINGS

Warnings: Consult a physician for use in children under 12 years of age. If pregnant or breast-feeding, ask a health professional before use. If symptoms persist or worsen, discontinue use and contact a health care professional.

- KEEP OUT OF THE REACH OF CHILDREN.

DOSAGE AND ADMINISTRATION

Directions: Adults and Children above 12 years: Shake 10 times before use. Spray 3 times under the tongue 2 times a day, on an empty stomach, or as directed by a health care professional.

Do not use if cap seal is broken.

Inactive ingredients: Ethyl alcohol 20%, Purified water.

QUESTIONS

Question or comments? Mfg. for: American Int. Group. Corp, Miami, FL 33141

MADE IN USA

For more information please visit. www.vidahomeopathy.com

http://naturalhairtreatments.blogspot.com/

PACKAGE LABEL

NDC: 66096-395-02

VIDA HOMEOPATHY

HAIR NOURISH Oral Spray

1 FL OZ (30mL) / 20% ALCOHOL

Purpose: Promotes healthy hair growth.